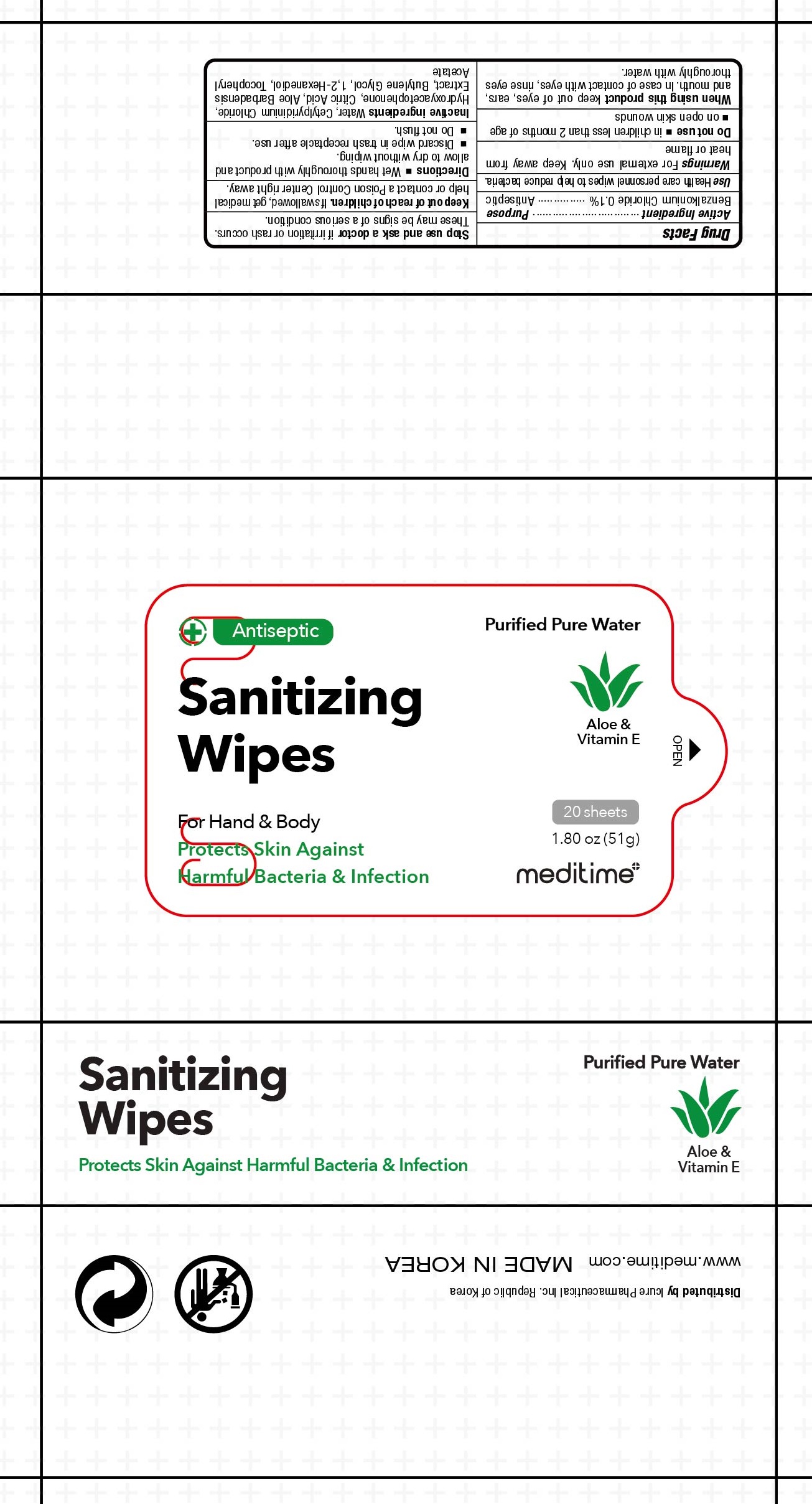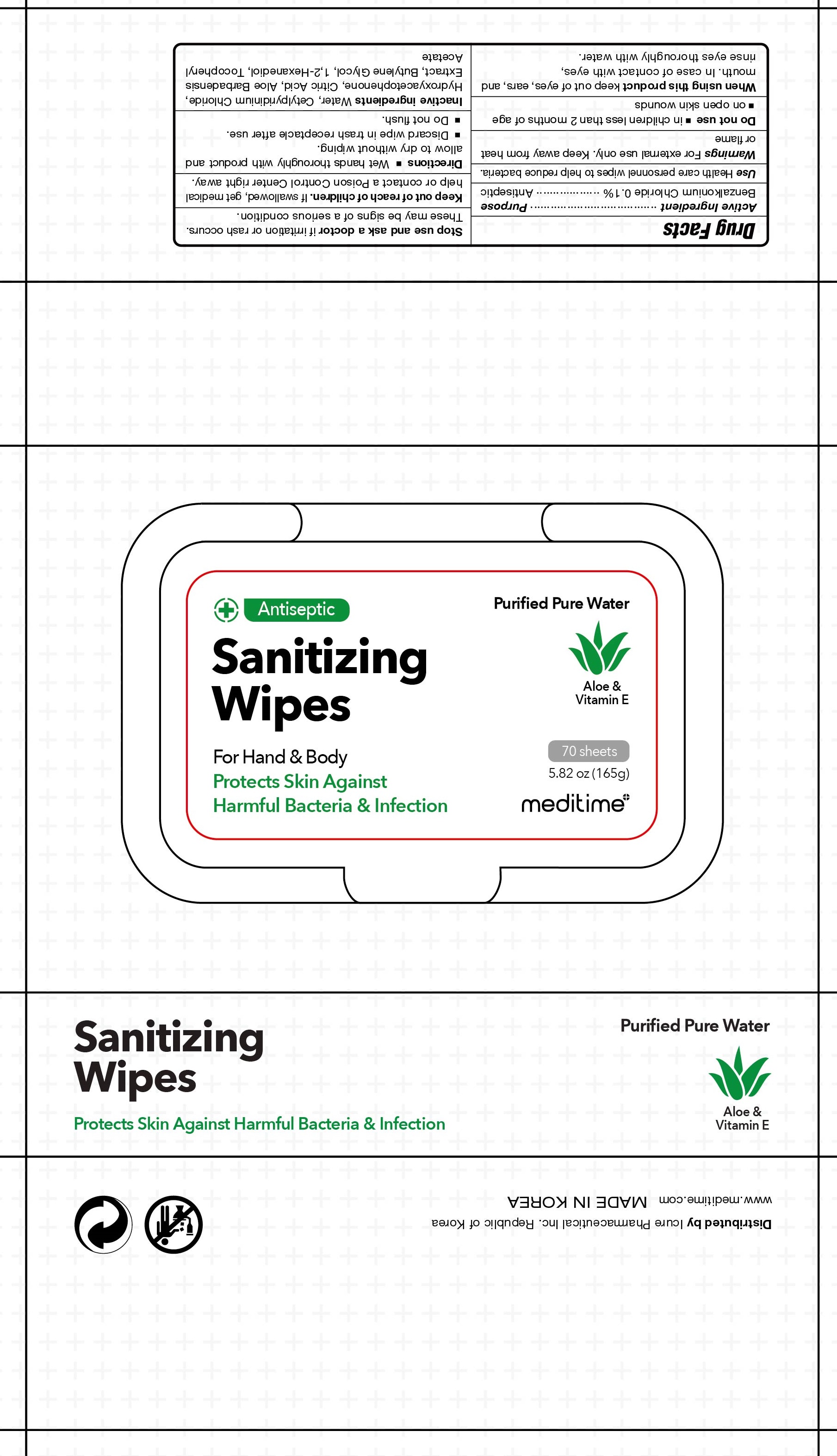 DRUG LABEL: Meditime Sanitizing Wipes
NDC: 73279-0003 | Form: CLOTH
Manufacturer: Icure Pharmaceutical Inc, Wanju Factory
Category: otc | Type: HUMAN OTC DRUG LABEL
Date: 20200617

ACTIVE INGREDIENTS: Benzalkonium Chloride 0.1 1/100 1
INACTIVE INGREDIENTS: WATER; CETYLPYRIDINIUM CHLORIDE; Hydroxyacetophenone; CITRIC ACID MONOHYDRATE; ALOE VERA LEAF; Butylene Glycol; 1,2-Hexanediol; .ALPHA.-TOCOPHEROL ACETATE

Drug Facts

ACTIVE INGREDIENT

Benzalkonium Chloride 0.1%

INACTIVE INGREDIENTS

Water, Cetylpyridinium Chloride, Hydroxyacetophenone, Citric Acid, Aloe Barbadensis Leaf Extract, Butylene Glycol, 1,2-Hexanediol, Tocopheryl Acetate

PURPOSE

ANTISEPTIC

WARNINGS

For external use only. Keep away from heat or flame
--------------------------------------------------------------------------------------------------------
Do not use
• in children less than 2 months of age
• on open skin wounds
--------------------------------------------------------------------------------------------------------
When using this product keep out of eyes, ears, and mouth. In case of contact with eyes, rinse eyes thoroughly with water.
--------------------------------------------------------------------------------------------------------
Stop use and ask a doctor if irritation or rash occurs. These may be signs of a serious condition.

KEEP OUT OF REACH OF CHILDREN

If swallowed, get medical help or contact a Poison Control Center right away.

Uses

Health care personnel wipes to help reduce bacteria.

Directions

■ Wet hands thoroughly with product and allow to dry without wiping
■ Discard wipe in trash receptacle after use
■ Do not flush